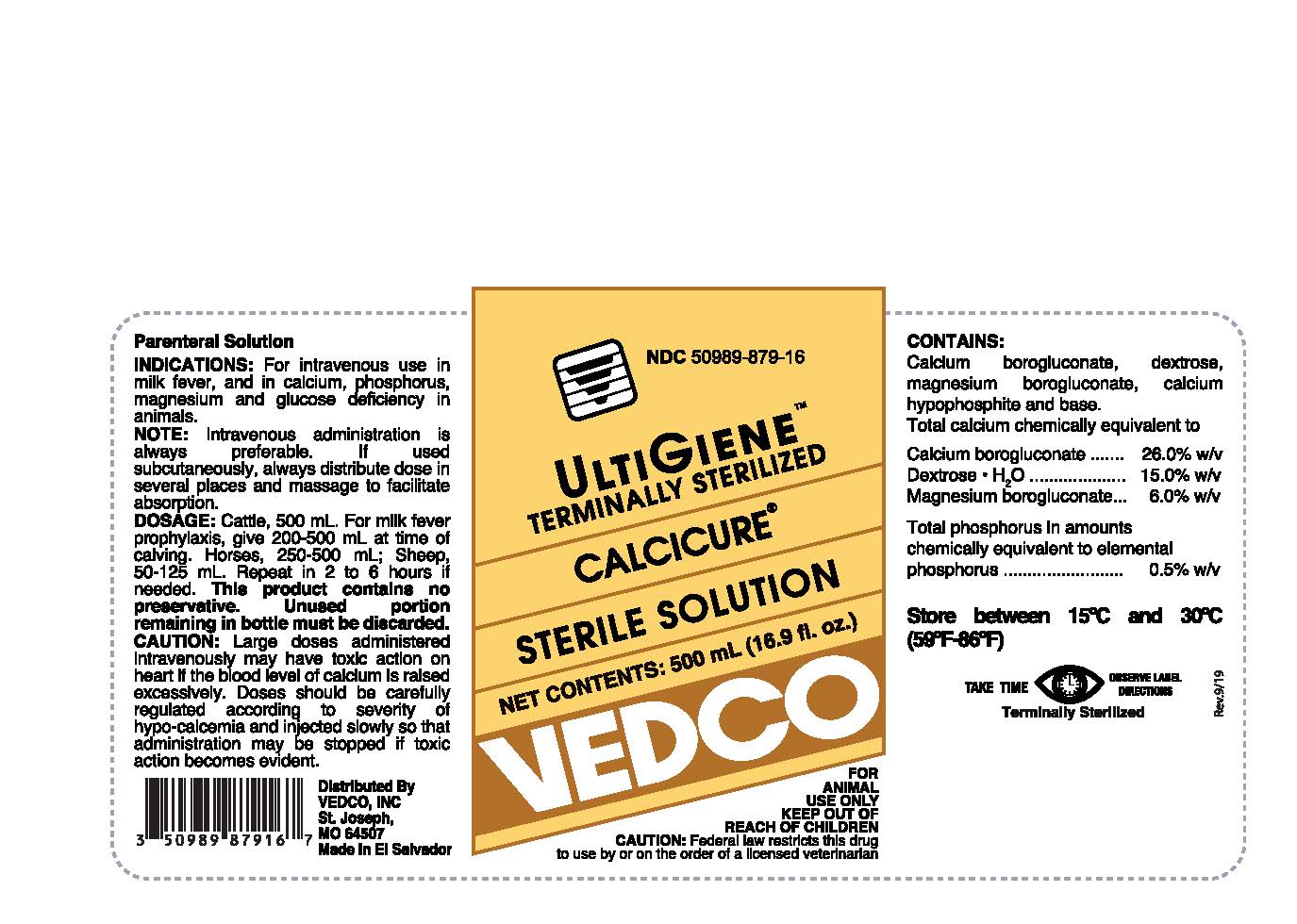 DRUG LABEL: CALCICURE
NDC: 50989-879 | Form: INJECTION, SOLUTION
Manufacturer: VEDCO, INC.
Category: animal | Type: PRESCRIPTION ANIMAL DRUG LABEL
Date: 20200703

ACTIVE INGREDIENTS: CALCIUM BOROGLUCONATE 26 g/100 mL; DEXTROSE MONOHYDRATE 15 g/100 mL; MAGNESIUM GLUCONATE 6 g/100 mL; PHOSPHORUS 0.5 g/100 mL

ULTIGIENE™ TERMINALLY STERILIZED CALCICURE® STERILE SOLUTION

VETERINARY INDICATIONS

Parenteral Solution

INDICATIONS:

For intravenous use in milk fever, and in calcium, phosphorous, magnesium and glucose deficiency in animals.

Note:

Intravenous administration is always preferable. If used subcutaneously, always distribute dose in several places and massage to facilitate absorption.

Dosage:

Cattle, 500 mL. For milk fever prophylaxis, give 200-500 mL at time of calving. Horses, 250-500 mL; Sheep, 50-125 mL. Repeat in 2 to 6 hours if needed. This product contains no preservative. Unused portion remaining in bottle must be discarded.

CAUTION:

Large doses administered intravenously may have toxic action on heart if the blood level of calcium is raised excessively. Doses should be carefully regulated according to severity of hypo-calcemia and injected slowly so that administration may be stopped if toxic action becomes evident.

PRECAUTIONS

FOR ANIMAL USE ONLY

KEEP OUT OF REACH OF CHILDREN

CAUTION:

Federal law restricts this drug to use by or on the order of a licensed veterinarian.

CONTAINS:

Calcium borogluconate, dextrose, magnesium borogluconate, calcium hypophosphite and base. Total calcium chemically equivalent to

Calcium borogluconate ....... 26.0% w/v

Dextrose • H2O .................. 15.0% w/v

Magnesium borogluconate ... 6.0% w/v

Total phosphorus in amounts chemically equivalent to elemental phosphorus .......... 0.5% w/v

STORAGE AND HANDLING

Store between 15°C and 30°C (59°F-86°F)

WARNINGS AND PRECAUTIONS

TAKE TIME OBSERVE LABEL DIRECTIONS

INFORMATION FOR OWNERS/CAREGIVERS

Terminally Sterilized

INFORMATION FOR OWNERS/CAREGIVERS

Distributed By

VEDCO, INC

St. Joseph,

MO 64507

Made in El Salvador

NDC 50989-879-16

Net Contents: 500 mL (16.9 fl. oz.)